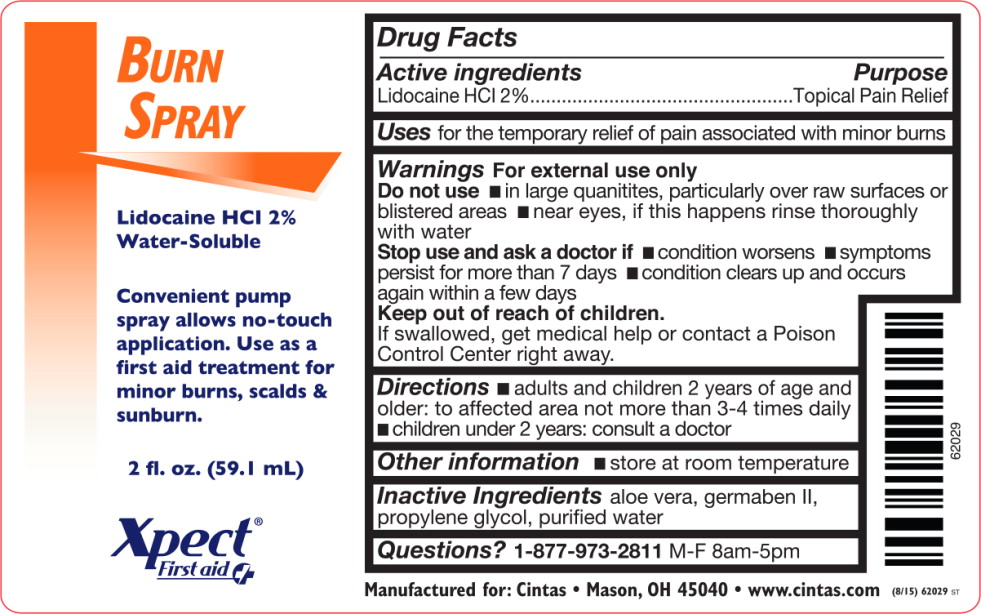 DRUG LABEL: Lidocaine Hydrochloride
NDC: 68421-5100 | Form: SPRAY
Manufacturer: Cintas First Aid & Safety
Category: otc | Type: HUMAN OTC DRUG LABEL
Date: 20150903

ACTIVE INGREDIENTS: Lidocaine Hydrochloride 20 g/1 L
INACTIVE INGREDIENTS: aloe vera leaf; propylene glycol; diazolidinyl urea; water

Drug Facts

Active Ingredient

Lidocaine HCl 2.0%

Purpose

Topical pain relief

Uses

for the temporary pain of relief associated with minor burns

Warnings

For external use only

Do not use

in large quantities, particularly over raw surfaces or blistered areas

- near eyes, if this happens rinse thoroughly with water

Stop use and ask doctor if

- condition worsens
- symptoms persist for more than 7 days
- condition clears up and occurs again within a few days

Keep out of reach of children. If swallowed get medical help or contact Poison Control Center right away.

Directions

- adults and children 2 years of age and older: to affected area not more than 3-4 times daily
- children under 2 years: consult a doctor

Other information

- store at room temperature

Inactive ingredients

aloe vera, germaben II, propylene glycol, purified water

Questions or Comments?

1-800-327-2704

Principal Display Panel - Bottle Label

Burn
Spray

Lidocaine HCl 2%
Water-Soluble

Convenient pump
spray allows no-touch
application. Use as a
first aid treatment for
minor burns, scalds &
sunburn.

2 fl. oz. (59.1 mL)

Xpect®
First aid